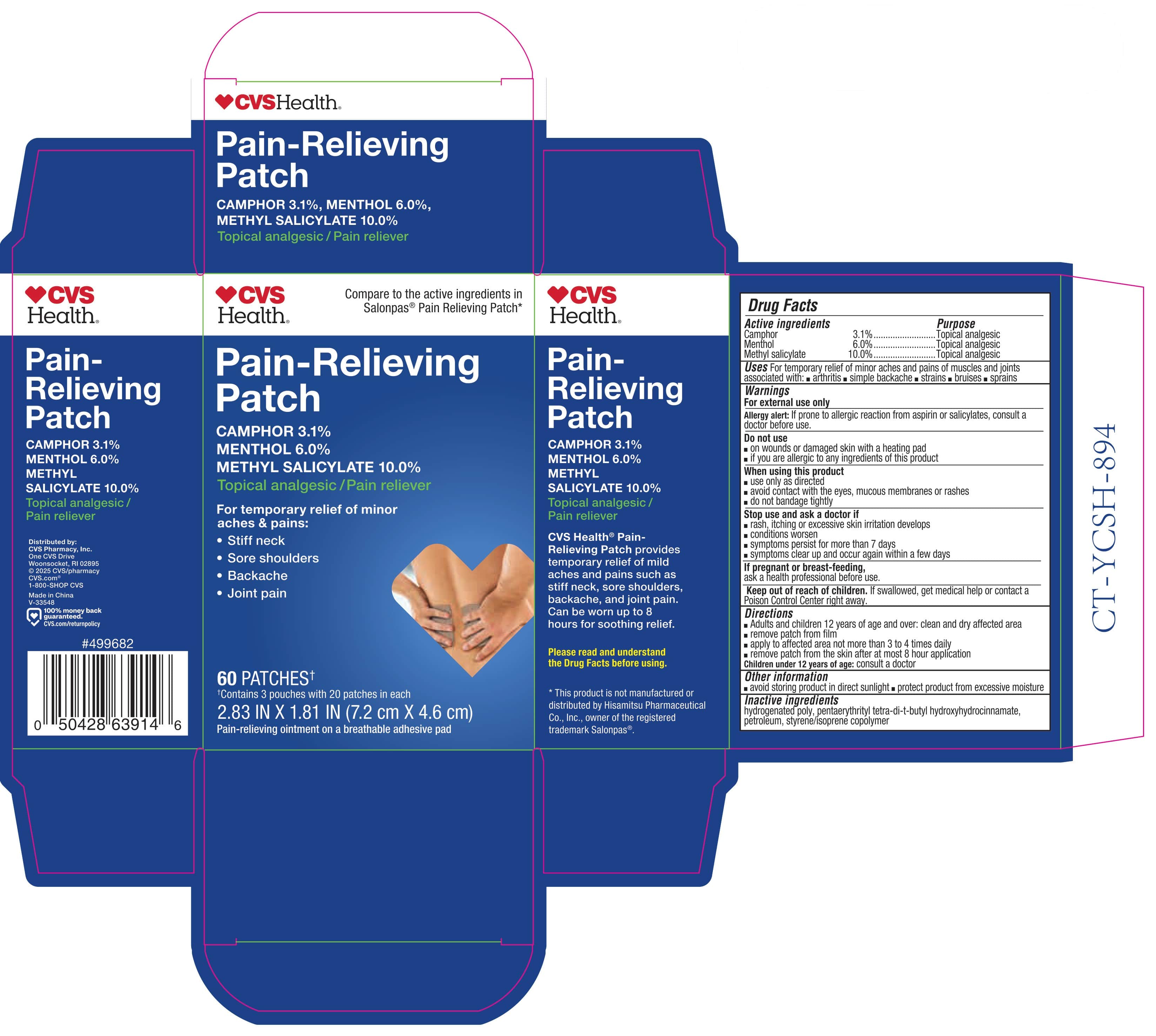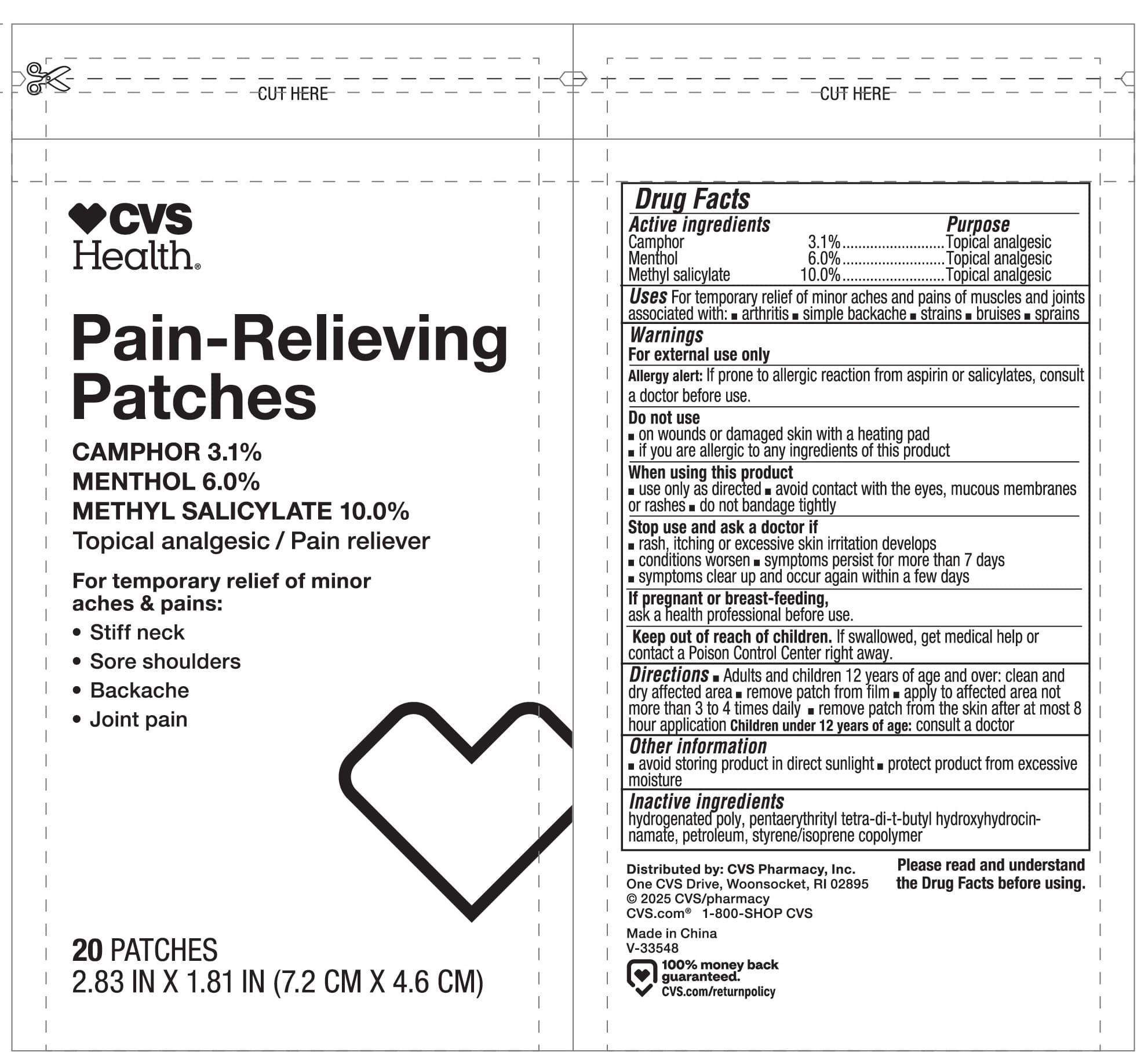 DRUG LABEL: CVS Health Pain Relieving
NDC: 66902-280 | Form: PATCH
Manufacturer: Natural Essentials, Inc.
Category: otc | Type: HUMAN OTC DRUG LABEL
Date: 20241204

ACTIVE INGREDIENTS: CAMPHOR (SYNTHETIC) 28 mg/1 1; MENTHOL, UNSPECIFIED FORM 54 mg/1 1; METHYL SALICYLATE 90 mg/1 1
INACTIVE INGREDIENTS: HYDROGENATED C6-20 POLYOLEFIN (100 CST); PENTAERYTHRITOL TETRAKIS(3-(3,5-DI-TERT-BUTYL-4-HYDROXYPHENYL)PROPIONATE); LIQUID PETROLEUM; STYRENE/ISOPRENE/STYRENE BLOCK COPOLYMER

Drug Facts

Active ingredients

Camphor 3.1%

Menthol 6.0%

Methyl salicylate 10.0%

Purpose

Topical analgesic

Topical analgesic

Topical analgesic

Uses

For temporary relief of minor aches and pains of muscles and joints associated with:

- arthritis
- simple backache
- strains
- bruises
- sprains

Warnings

For external use only

Allergy alert:If prone to allergic reaction from aspirin or salicylates, consult a doctor before use.

Do not use

- on wounds or damaged skin with a heating pad
- if you are allergic to any ingredients of this product

When using this product

- use only as directed
- avoid contact with the eyes, mucous membranes or rashes
- do not bandage tightly

Stop use and ask a doctor if

- rash, itching or excessive skin irritation develops
- conditions worsen
- symptoms persist for more than 7 days
- symptoms clear up and occur again within a few days

If pregnant or breast-feeding,

ask a health professional before use.

Keep out of reach of children.If swallowed, get medical help or contact a Poison Control Center right away.

Directions

- Adults and children 12 years of age and over: clean and dry affected area
- remove patch from film
- apply to affected area not more than 3 to 4 times daily
- remove patch from the skin after at most 8 hour application

Children under 12 years of age: consult a doctor

Other information

- avoid storing product in direct sunlight
- protect product from excessive moisture

Inactive ingredients

hydrogenated poly, pentaerythrityl tetra-di-t-butyl hydroxyhydrocinnamate, petroleum, styrene/isoprene copolymer

Principal Display Panel - 60 Patch Box Label

CVS
Health®

Compare to the active ingredients in
Salonpas® Pain Relieving Patch*

Pain-Relieving
Patch

CAMPHOR 3.1%

MENTHOL 6.0%

METHYL SALICYLATE 10.0%

Topical analgesic/Pain reliever

For temporary relief of minor
aches & pains:

- Stiff neck
- Sore shoulders
- Backache
- Joint pain

60 PATCHES†

†Contains 3 pouches with 20 patches in each

2.83 IN X 1.81 IN (7.2 cm X 4.6 cm)

Pain-relieving ointment on a breathable adhesive pad

Principal Display Panel - 20 Patch Pouch Label

CVS
Health®

Pain-Relieving
Patches

CAMPHOR 3.1%

MENTHOL 6.0%

METHYL SALICYLATE 10.0%

Topical analgesic/Pain reliever

For temporary relief of minor
aches & pains:

- Stiff neck
- Sore shoulders
- Backache
- Joint pain

20 PATCHES

2.83 IN X 1.81 IN (7.2 CM X 4.6 CM)